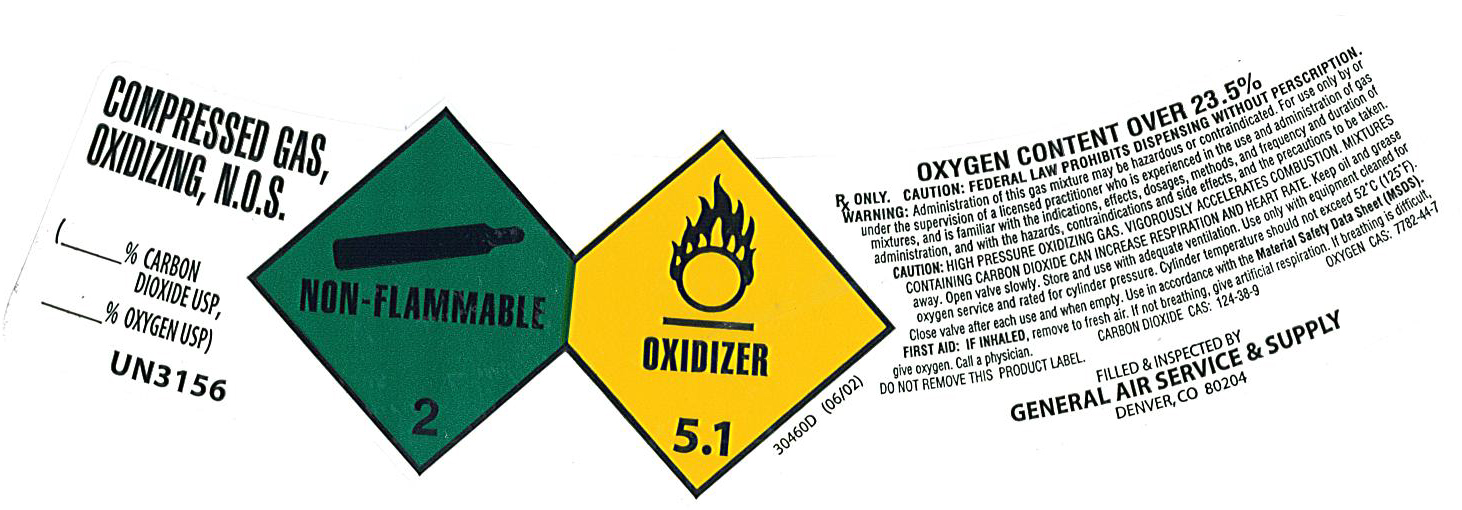 DRUG LABEL: Carbon Dioxide Oxygen Mixture
NDC: 21220-129 | Form: GAS
Manufacturer: General Air Service & Supply Co
Category: prescription | Type: HUMAN PRESCRIPTION DRUG LABEL
Date: 20101007

ACTIVE INGREDIENTS: Carbon Dioxide 200 mL/1 L; Oxygen 800 mL/1 L

carbon dioxide oxygen mixture

PACKAGE LABEL

COMPRESSED GAS, OXIDIZING, N.O.S.
(% CARBON DIOXIDE USP, %OXYGEN USP) UN 3156 NON-FLAMMABLE 2 OXIDIZER 5.1 30460D (06/02)
OXYGEN CONTENT OVER 23.5% Rx only. CAUTION: FEDERAL LAW PROHIBITS DISPENSING WITHOUT A PRESCRIPTION. WARNING: Administration of this gas may be hazardous or contraindicated. For use only by under the supervision of a licensed practitioner who is experienced in the use and administration of gas mixtures and is familiar with the indications, effects, dosages, methods, and frequency and duration of administration, and with the hazards, contraindication and side effects, and the precautions to be taken. CAUTION: HIGH PRESSURE OXIDIZING GAS. VIGOROUSLY ACCELERATES COMBUSTION. MIXTURES CONTAINING CARBON DIOXIDE CAN INCREASE RESPIRATION AND HEART RATE. Keep oil and grease away. Open valve slowly. Store and use with adequate ventilation. Use only with equipment cleaned for oxygen service and rated for cylinder pressure. Cylinder temperature should not exceed 52C (125F). Close valve after each use and when empty. Use in accordance with the Material Safety Data Sheet (MSDS). FIRST AID: IF INHALED, remove to fresh air. If not breathing, give artificial respiration. If breathing is difficult, give oxygen. Call a physician. CARBON DIOXIDE CAS: 124-38-9 OXYGEN CAS: 7782-44-7 DO NOT REMOVE THIS PRODUCT LABEL.
FILLED and INSPECTED BY GENERAL AIR SERVICE and SUPPLY DENVER, CO 80204